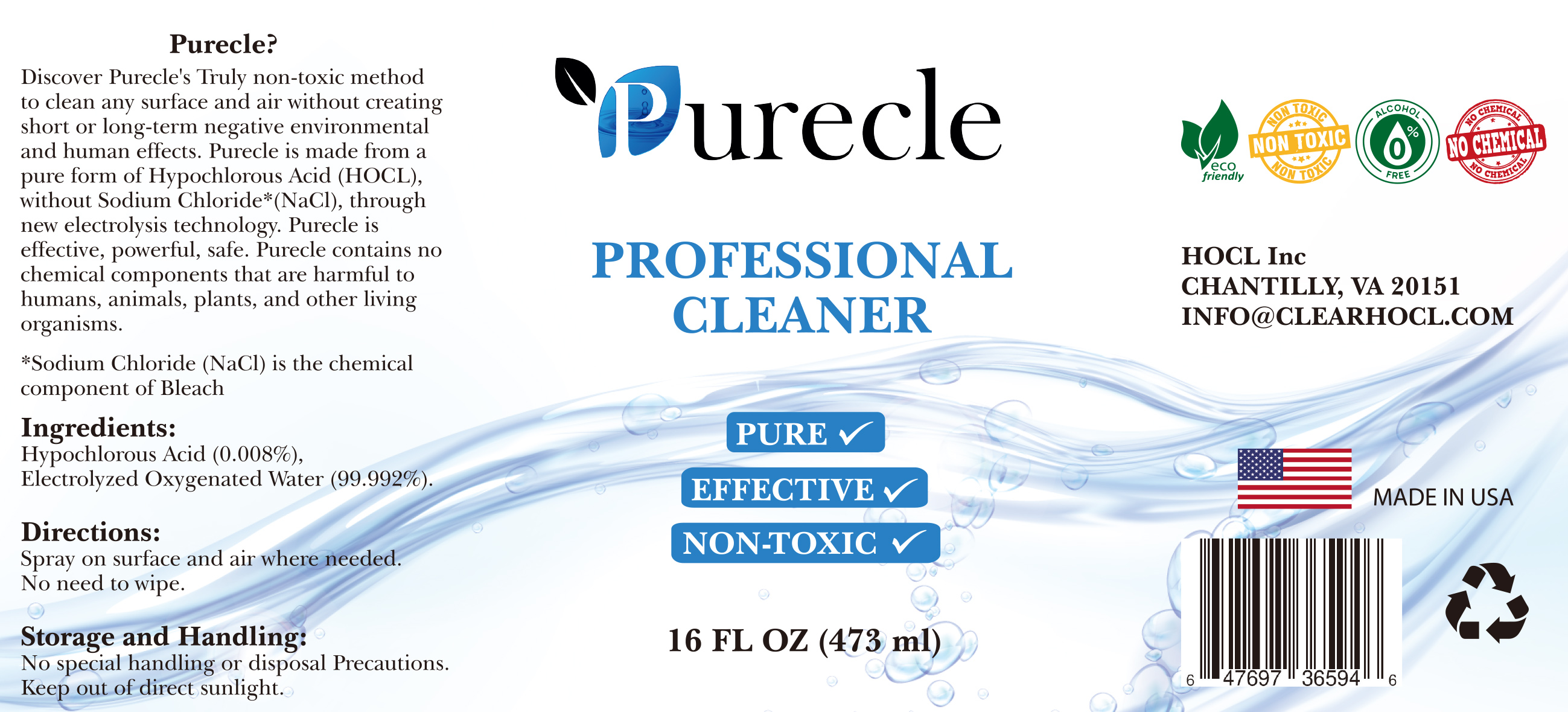 DRUG LABEL: PURECLE
NDC: 81270-201 | Form: SPRAY
Manufacturer: HOCL inc.
Category: otc | Type: HUMAN OTC DRUG LABEL
Date: 20210118

ACTIVE INGREDIENTS: HYPOCHLOROUS ACID 0.008 g/0.008 g
INACTIVE INGREDIENTS: WATER 0.00092 g/0.008 g

ACTIVE INGREDIENT

Hypochlorous Acid

INACTIVE INGREDIENT

Water

KEEP OUT OF REACH OF THE CHILDREN

PURPOSE

Immediately effective on various bacteria (i.e. odor causing bacteria), viruses, and fungi

DOSAGE AND ADMINISTRATION

For external use only

INDICATIONS AND USAGE

Spray proper amount to the product

WARNINGS

For external use only.